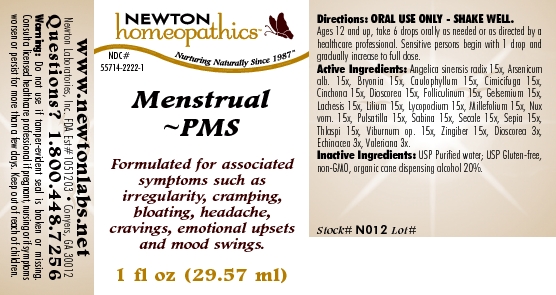 DRUG LABEL: Menstrual - PMS   
NDC: 55714-2222 | Form: LIQUID
Manufacturer: Newton Laboratories, Inc.
Category: homeopathic | Type: HUMAN OTC DRUG LABEL
Date: 20110301

ACTIVE INGREDIENTS: Angelica Sinensis Root 15 [hp_X]/1 mL; Arsenic Trioxide 15 [hp_X]/1 mL; Bryonia Alba Root 15 [hp_X]/1 mL; Caulophyllum Thalictroides Root 15 [hp_X]/1 mL; Black Cohosh 15 [hp_X]/1 mL; Cinchona Officinalis Bark 15 [hp_X]/1 mL; Dioscorea Villosa Tuber 15 [hp_X]/1 mL; Estrone 15 [hp_X]/1 mL; Gelsemium Sempervirens Root 15 [hp_X]/1 mL; Lachesis Muta Venom 15 [hp_X]/1 mL; Lilium Lancifolium Whole Flowering 15 [hp_X]/1 mL; Lycopodium Clavatum Spore 15 [hp_X]/1 mL; Achillea Millefolium 15 [hp_X]/1 mL; Strychnos Nux-vomica Seed 15 [hp_X]/1 mL; Pulsatilla Vulgaris 15 [hp_X]/1 mL; Juniperus Sabina Leafy Twig 15 [hp_X]/1 mL; Claviceps Purpurea Sclerotium 15 [hp_X]/1 mL; Sepia Officinalis Juice 15 [hp_X]/1 mL; Capsella Bursa-pastoris 15 [hp_X]/1 mL; Viburnum Opulus Bark 15 [hp_X]/1 mL; Ginger 15 [hp_X]/1 mL; Echinacea, Unspecified 3 [hp_X]/1 mL; Valerian 3 [hp_X]/1 mL
INACTIVE INGREDIENTS: Alcohol

Menstrual - PMS

INDICATIONS & USAGE SECTION

Menstrual - PMS Formulated for associated symptoms such as irregularity, cramping, bloating, headache, cravings, emotional upsets and mood swings.

DOSAGE & ADMINISTRATION SECTION

Directions: ORAL USE ONLY - SHAKE WELL. Ages 12 and up, take 6 drops orally as needed or as directed by a healthcare professional. Sensitive persons begin with 1 drop and gradually increase to full dose.

OTC - ACTIVE INGREDIENT SECTION

Angelica sinensis radix 15x, Arsenicum alb. 15x, Bryonia 15x, Caulophyllum 15x, Cimicifuga 15x, Cinchona 15x, Dioscorea 15x, Folliculinum 15x, Gelsemium 15x, Lachesis 15x, Lilium 15x, Lycopodium 15x, Millefolium 15x, Nux vom. 15x, Pulsatilla 15x, Sabina 15x, Secale 15x, Sepia 15x, Thlaspi 15x, Viburnum op. 15x, Zingiber 15x, Dioscorea 3x, Echinacea 3x, Valeriana 3x.

OTC - PURPOSE SECTION

Formulated for associated symptoms such as irregularity, cramping, bloating, headache, cravings, emotional upsets and mood swings.

INACTIVE INGREDIENT SECTION

Inactive Ingredients: USP Purified Water; USP Gluten-free, non-GMO, organic cane dispensing alcohol 20%.

QUESTIONS SECTION

www.newtonlabs.net Newton Laboratories, Inc. FDA Est # 1051203 - Conyers, GA 30012
Questions? 1.800.448.7256

WARNINGS SECTION

Warning: Do not use if tamper - evident seal is broken or missing. Consult a licensed healthcare professional if pregnant, nursing or if symptoms worsen or persist for more than a few days. Keep out of reach of children.

OTC - PREGNANCY OR BREAST FEEDING SECTION

Consult a licensed healthcare professional if pregnant, nursing or if symptoms worsen or persist for more than a few days.

OTC - KEEP OUT OF REACH OF CHILDREN SECTION

Keep out of reach of children.